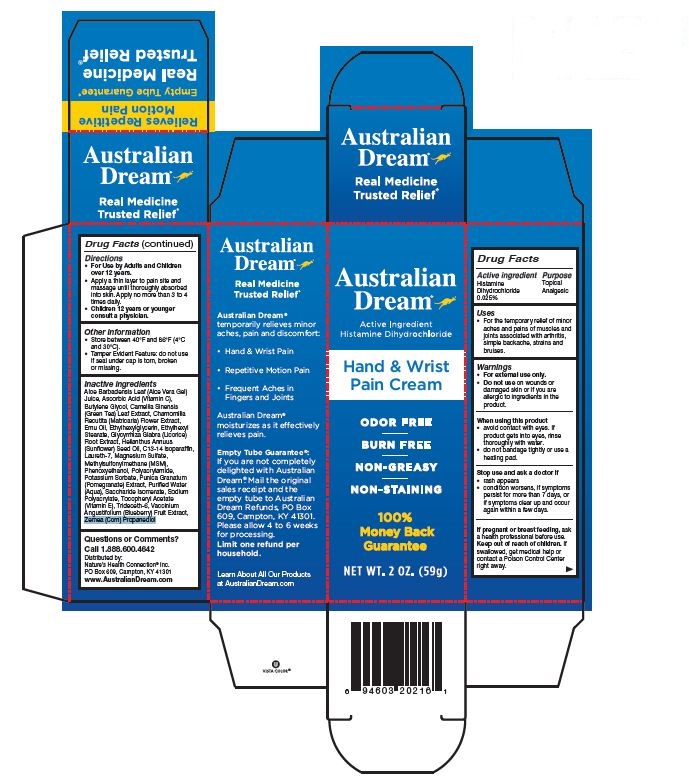 DRUG LABEL: Hand and Wrist Pain Cream
NDC: 61577-8122 | Form: CREAM
Manufacturer: Sombra Cosmetics, Inc.
Category: otc | Type: HUMAN OTC DRUG LABEL
Date: 20191209

ACTIVE INGREDIENTS: HISTAMINE DIHYDROCHLORIDE .00025 g/1 g
INACTIVE INGREDIENTS: ALOE VERA LEAF; Water; ASCORBIC ACID; BUTYLENE GLYCOL; CAMELLIA SINENSIS FLOWER; MATRICARIA CHAMOMILLA; EMU OIL; ETHYLHEXYLGLYCERIN; ETHYLHEXYL STEARATE; GLYCYRRHIZA GLABRA; SUNFLOWER OIL; C13-14 ISOPARAFFIN; LAURETH-7; MAGNESIUM SULFATE, UNSPECIFIED; DIMETHYL SULFONE; PHENOXYETHANOL; POLYACRYLAMIDE (10000 MW); POTASSIUM SORBATE; PUNICA GRANATUM SEED; SACCHARIDE ISOMERATE; SODIUM POLYACRYLATE (8000 MW); TOCOPHEROL; TRIDECETH-6; VACCINIUM ANGUSTIFOLIUM WHOLE; PROPANEDIOL

Hand and Wrist Pain Cream

Active Ingredients

Histamine Dihydrochloride 0.025%

Keep out of reach of children

If swallowed, get medical help or contact a Poison Control Center right away

PURPOSE

Topical Analgesic

Uses

For temporary relief of minor aches and pains of muscles and joints associated with arthritis, simple backache, strains and bruises

Warnings

For external use only. Do not use on wounds or damaged skin or if you are allergic to ingredients in this product. When using this product: avoid contact with eyes. If product gets into eyes, rinse thoroughly with water. Do not bandage tightly or use a heating pad.

Stop use and ask doctor if: rash appears. Condition worsens. If symptoms persist for more than 7 days or if symptoms clear up and occur again within a few days.

If pregnant or breast feeding, ask a health professional before use.

Directions

For Use by Adults and Children over 12 years. Apply a thin layer to pain site and massage until thoroughly absorbed into skin. Apply no more than 3 to 4 times daily.

Children 12 years or younger consult a physician

Inactive Ingredients

Aloe Barbadensis Leaf (Aloe Vera Gel), Aqua (Purified Water), Ascorbic Acid (Vitamin C), Butylene Glycol, Camellia Sinensis (Green Tea) Leaf Extract, Chamomilla Recutita (Matricaria) Flower Extract, Emu Oil, Ethylhexylglycerin, Ethylhexyl Stearate, Glycyrrhiza Glabra (Licorice) Root Extract, Helianthus Annuus (Sunflower) Seed Oil, C13-14 Isoparaffin, Laureth-7, Magnesium Sulfate, Methylsulfonylmethane (MSM), Phenoxyethanol, Polyacrylamide, Potassium Sorbate, Purica Granatum (Pomegranate) Extract, Saccharide Isomerate, Sodium Polyacrylate, Tochopheryl Acetate (Vitamin E), Trideceth-6, Vaccinium Angustifolium (Blueberry) Fruit Extract, Zemea (Corn) Propanediol

Questions or Comments?

Call 1-888-600-4642